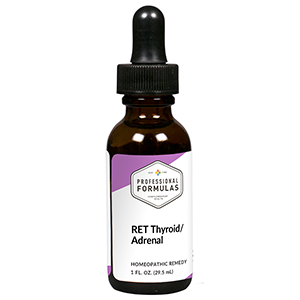 DRUG LABEL: RET Thyroid/Adrenal
NDC: 63083-7011 | Form: LIQUID
Manufacturer: Professional Complementary Health Formulas
Category: homeopathic | Type: HUMAN OTC DRUG LABEL
Date: 20190815

ACTIVE INGREDIENTS: POPULUS TREMULA FLOWERING TOP 3 [hp_X]/29.5 mL; SCLERANTHUS ANNUUS FLOWERING TOP 3 [hp_X]/29.5 mL; CALCIUM SULFATE ANHYDROUS 3 [hp_X]/29.5 mL; MAGNESIUM PHOSPHATE, DIBASIC TRIHYDRATE 3 [hp_X]/29.5 mL; SILICON DIOXIDE 3 [hp_X]/29.5 mL; STRYCHNOS IGNATII SEED 30 [hp_X]/29.5 mL; IODINE 30 [hp_X]/29.5 mL; LYCOPODIUM CLAVATUM SPORE 30 [hp_X]/29.5 mL; NUTMEG 30 [hp_X]/29.5 mL; SMILAX ORNATA ROOT 30 [hp_X]/29.5 mL; ZINC 30 [hp_X]/29.5 mL
INACTIVE INGREDIENTS: ALCOHOL; WATER

RET11

ACTIVE INGREDIENTS

Aspen flower essence 3X
Scleranthus flower essence 3X
Calcarea sulphurica 3X, 6X, 30X
Magnesia phosphorica 3X, 6X, 30X
Silicea 3X, 6X, 30X
and all the following at 30X, 100X, 200X:
Ignatia amara
Iodium
Lycopodium clavatum
Nux moschata
Sarsaparilla
Zincum metallicum

QUESTIONS

Professional Formulas

PO Box 2034 Lake Oswego, OR 97035

INDICATIONS

Temporarily relieves indecision, uncertainty, fear and worry of the unknown, anxiousness, or oversensitivity.*

PURPOSE

*Claims based on traditional homeopathic practice, not accepted medical evidence. Not FDA evaluated.

WARNINGS

In case of overdose, get medical help or contact a poison control center right away.

Keep out of the reach of children.

PREGNANCY OR BREAST FEEDING

If pregnant or breastfeeding, ask a healthcare professional before use.

DIRECTIONS

Place drops under tongue 30 minutes before/after meals. Adults and children 12 years and over: Take 5 drops up to 4 times per day for up to one month. Consult a physician for use in children under 12 years of age.

OTHER INFORMATION

Tamper resistant. If seal is broken, do not use. After opening, close container tightly and store at room temperature away from heat.

INACTIVE INGREDIENTS

20% ethanol, purified water.

LABEL

Est 1985

Professional Formulas

Complementary Health

RET Thyroid/Adrenal

Homeopathic Remedy

1 FL. OZ. (29.5 mL)